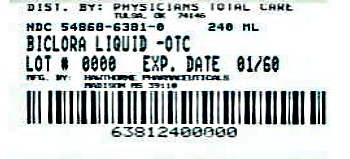 DRUG LABEL: biclora
                        
NDC: 54868-6381 | Form: LIQUID
Manufacturer: Physicians Total Care, Inc.
Category: otc | Type: HUMAN OTC DRUG LABEL
Date: 20130102

ACTIVE INGREDIENTS: Chlophedianol Hydrochloride 12.5 mg/5 mL; Chlorcyclizine Hydrochloride 12.5 mg/5 mL
INACTIVE INGREDIENTS: Citric Acid Monohydrate; Glycerin; Propylene Glycol; Water; Sodium Citrate; Sorbitol; Sucralose

biclora Liquid

Drug Facts

Active ingredients
(in each 5 mL teaspoonful)
Chlophedianol Hydrochloride 12.5 mg
Chlorcyclizine Hydrochloride 12.5 mg

Purpose

Antitussive
Antihistamine

Uses

Temporarily relieves these symptoms due to the common cold, hay fever (allergic rhinitis) or other upper respiratory allergies:

- cough due to minor throat and bronchial irritation
- calms the cough control center and relieves coughing
- runny nose
- sneezing
- itching of the nose or throat
- itchy, watery eyes

Warnings

Ask a doctor before use if you have

- a cough that lasts or is chronic such as occurs with smoking, asthma or emphysema
- a cough that occurs with too much phlegm (mucus)
- a breathing problem such as emphysema or chronic bronchitis
- glaucoma
- difficulty in urination due to the enlargement of the prostate gland

Ask a doctor or pharmacist before use if you are taking sedatives or tranquilizers.

When using this product

- excitability may occur, especially in children
- may cause marked drowsiness
- avoid alcoholic drinks
- alcohol, sedatives, and tranquilizers may increase the drowsiness effect
- be careful when driving a motor vehicle or operating machinery

Stop use and ask a doctor if

- cough persists for more than 1 week, tends to recur, or is accompanied by a fever, rash, or persistent headache. A persistent cough may be a sign of a serious condition
- new symptoms occur

Keep out of reach of children.

In case of overdose, get medical help or contact a Poison Control Center immediately.

Directions

Do not exceed recommended dosage.
Use a calibrated measuring device for administering the drug to a child.

Adults and children 12 years of age and over: | 2 teaspoonfuls (10 mL) every 6 to 8 hours, not to exceed 6 teaspoonfuls in 24 hours, or as directed by a doctor.
Children 6 to under 12 years of age: | 1 teaspoonful (5 mL) every 6 to 8 hours, not to exceed 3 teaspoonfuls in 24 hours, or as directed by a doctor.
Children under 6 years of age: | Consult a doctor.

Other information

Store at 20°-25°C (68°-77°F); excursions permitted to 15°-30°C (59°-86°F).
[See USP Controlled Room Temperature].

Inactive ingredients

Cherry Flavor, Citric Acid, Glycerin, Propylene Glycol, Purified Water, Sodium Citrate, Sorbitol, Sucralsoe.

Questions? Comments?

To report a serious adverse event or obtain product information, contact
1-888-455-5253.
Manufactured for:
Hawthorn Pharmaceuticals,
Madison, MS 39110
HI282 Rev. 12/11

Product Packaging

The packaging below represents the labeling currently used.
Principal display panel for 8 fl oz. label:
NDC 54868-6381-0
biclora LIQUID
Antitusive · Antihistamine
Each teaspoonful (5 mL) contains:
Chlophedianol HCl.......................12.5 mg
Chlorcyclizine HCl.......................12.5 mg
For professional use.
The labeling for this product includes professional labeling
which is not intended for use by the general public.
Patent Pending
Alcohol Free · Dye Free
Cherry Flavor
HAWTHORN
PHARMACEUTICALS, INC.
8 fl oz (240 mL)
Distributed by:
Physicians Total Care, Inc.
Tulsa, OK 74146